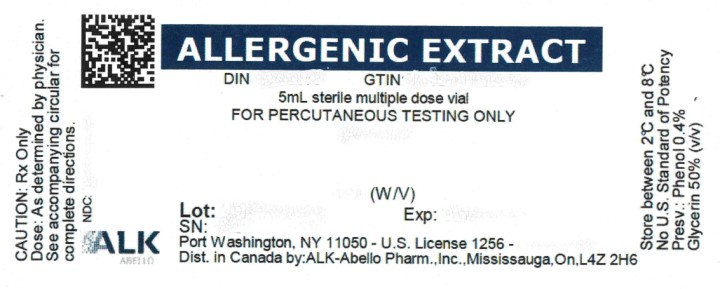 DRUG LABEL: ALMOND
NDC: 0268-6100 | Form: INJECTION, SOLUTION
Manufacturer: ALK-Abello, Inc.
Category: other | Type: NON-STANDARDIZED ALLERGENIC LABEL
Date: 20250804

ACTIVE INGREDIENTS: ALMOND 0.1 g/1 mL
INACTIVE INGREDIENTS: SODIUM CHLORIDE; PHENOL; GLYCERIN

Food Allergenic Extracts

ALLERGENIC EXTRACTS,

FOR DIAGNOSTIC USE ONLY

DIRECTIONS FOR USE

WARNING

This product is intended for use by physicians who are experienced in the administration of allergenic extracts and the emergency care of anaphylaxis, or for use under the guidance of an allergy specialist.

As with all allergenic extracts, severe systemic reactions may occur. In certain individuals these life-threatening reactions may result in death. Fatalities associated with skin testing have been reported. Patients should be observed for at least 20 - 30 minutes following testing. Emergency measures and adequately trained personnel should be immediately available in the event of a life-threatening reaction.

Patients with unstable asthma or steroid dependent asthmatics and patients with underlying cardiovascular disease are at greater risk to a fatal outcome from a systemic allergic reaction.

Sensitive patients may experience severe anaphlactic reactions resulting in respiratory obstruction, shock, coma and/or death. Adverse events are to be reported to MedWatch (1-800-FDA-1088), Adverse Event Reporting, Food and Drug Administration, 5600 Fishers Lane, Rockville, MD 20852-9787. This product should not be injected intravenously. Patients receiving beta blockers may not be responsive to epinephrine or inhaled bronchodilators. Respiratory obstruction not responding to parenteral or inhaled bronchodilators may require theophylline, oxygen, intubation and the use of life support systems. Parenteral fluid and/or plasma expanders may be utilized for the treatment of shock. Adrenocorticosteroids may be administered parenterally or intravenously. Refer to WARNINGS, PRECAUTIONS, and ADVERSE REACTIONS sections below.

Port Washington, NY 11050

U.S. Government License No. 1256

DESCRIPTION

Sterile diagnostic extracts are supplied in either phenol-saline diluent for Intradermal Testing or in diluent containing glycerin 50% (v/v) for Percutaneous Testing and phenol 0.4% (preservative). Inactive ingredients may include: sodium chloride for isotonicity, glycerin, and sodium bicarbonate as a buffer.

Pollens are individually extracted from pure pollen extracted in a phenol-preserved sodium bicarbonate solution. Short Ragweed and Mixed (Tall and Short) Ragweed extracts are standardized by Antigen E content and so labeled. The Antigen E content of extracts containing Short Ragweed at a concentration more dilute than a weight/volume ratio of 1:10 are obtained by calculating the Antigen E content based on the assay value of more concentrated extract. Pollen extracts are filtered aseptically and after final packaging, they are tested for sterility and safety. Molds are individwually extracted from pure powdered inactivated mold source material extracted in phenol preserved saline. Mold extracts are filtered aseptically and after final packaging are tested for sterility and safety.

Molds (fungi) are present in all inhabited places at all seasons of the year; they are so ubiquitous that they are prevalent at times when common allergic pollens and other inhalants are not. In the home and surroundings, molds are found in upholstered furniture, mattresses, drapes, cellar and storage room dust, woolens, leather goods, fruits, meats, cheeses, garden soil and on plants. Spores, mycelial fragments and mold residues are thus inhaled, contacted and ingested continuously.

Foods, miscellaneous inhalants and epidermals are individually extracted in phenol preserved saline or glycerin, filtered aseptically and after final packaging are tested for sterility and safety.

CLINICAL PHARMACOLOGY

Diagnostically (for skin testing) the allergen combines with IgE antibodies fixed to mast cells in the skin. This complexing causes an increase in cellular permeability and degranulation of the mast cells releasing chemical mediators. These mediators (such as histamine) are responsible for a local inflammatory response of wheal and erythema typical of a positive skin test reaction and also, the symptoms commonly associated with allergic disease.^1 The more mediator release, the larger the reaction (wheal and erythema).

INDICATIONS AND USAGE

These products are for diagnostic use only. Diagnostic allergenic extracts are indicated for use in skin testing to establish the clinical relevance of specific allergens to which the patient has been exposed. By measuring skin test response, the physician may assess the degree of sensitivity that patients have to the allergens. For extracts standardized in AU and BAU, see individual directions for use. Allergenic extracts for diagnostic use only of coffee, mosquito, cottonseed, and flaxseed have not been shown by adequate data to be safe and effective for therapeutic use.

CONTRAINDICATIONS

Patients on beta blockers can be non-responsive to beta agonists that may be required to reverse a systemic reaction (also, see boxed WARNING statement and ADVERSE REACTIONS). The physician should carefully weigh the benefit derived from skin testing vs. the risk to the patient should a systemic reaction arise.

Patients with unstable asthma or steroid dependent asthmatics and patients with underlying cardiovascular disease are at greater risk to a fatal outcome from a systemic allergic reaction^2,3. See also PRECAUTIONS and ADVERSE REACTIONS.

WARNINGS

Severe Allergic Reactions:

Patients should always be observed for at least 20 - 30 minutes after skin testing. In the event of a marked systemic reaction such as urticaria, angioedema, wheezing, dyspnea, respiratory obstruction, hypotension, coma and death (see ADVERSE REACTIONS), applications of a tourniquet above the injection site and administration of 0.2 mL to 1 mL (0.01 mg/kg) of epinephrine injection (1:1,000) are recommended. Maximal recommended dose for children between 2 and 12 years of age is 0.5 mL. The tourniquet is then gradually released at 15-minute intervals. Patients under treatment with beta blockers may be refractory to the usual dose of epinephrine.

Volume expanders and vasopressor agents may be required to reverse hypotension, inhalation bronchodilators and parenteral aminophylline may be required to reverse bronchospasm. In case of respiratory obstruction, oxygen and intubation may be necessary. Life-threatening reactions unresponsive to the above may require cardiopulmonary resuscitation.

Anaphylaxis Following False Negative Food Allergen Skin Test Results:

False negative skin test results associated with anaphylaxis from subsequent exposure to the allergen have been reported during postmarketing diagnostic use of some food allergenic extracts. Based on the patient’s clinical history and the index of suspicion, healthcare providers should consider confirming negative skin testing with serologic testing by measuring specific serum IgE or with a medically-supervised oral food challenge.

INFORMATION FOR PATIENTS:

Patients should be instructed to describe any active allergic symptoms such as rhinitis, wheezing, dyspnea, etc. prior to testing. Also, see ADVERSE REACTIONS and WARNINGS Sections.

Patients should always be observed 20 to 30 minutes after testing.

General:

1. In the presence of active symptoms such as rhinitis, wheezing, dyspnea, etc., the indications for skin testing must be weighed carefully against the risk of temporarily aggravating the symptoms by the testing itself. Objective assessment of pulmonary function such as Peak Expiratory Flow Rate (PEFR) before allergen administration and prior to discharge may be useful in unstable asthmatics to reduce the chances of exacerbation of the patient’s asthma. Patients should be instructed to describe any active allergic symptoms as described above prior to skin testing and encouraged to report any late reactions from this testing. Also, see ADVERSE REACTIONS and WARNING sections.
2. Store allergenic extracts between 2°-8°C at all times, even during use.
3. Care must be taken to avoid drawing blood.
  1. For percutaneous testing, if blood is observed, immediately wipe the allergen from the site.
  2. For intradermal skin testing, pull gently on the syringe plunger and note if any blood enters the syringe. If blood is obtained, reposition the needle and repeat before injecting (see DOSAGE AND ADMINISTRATION).
4. Allergenic extracts become less potent with age. Allergenic extracts containing glycerin 50% v/v are relatively stable. Non-glycerinated aqueous extracts, particularly dilute forms as used for intradermal skin testing, have been shown to be extremely unstable. Until such time as stability studies are complete with dilute allergens, new intradermal strength materials should be prepared every few weeks.
5. Use standard aseptic precautions if making dilutions from stock concentrates to intradermal strength.
6. For intradermal testing: Extracts in glycerin 50% v/v must be diluted with a non-glycerinated diluent and must be diluted at least 25-fold to less than 2% glycerin by volume, as glycerin above this level can cause false positive intradermal skin test results.

Pregnancy - Category C:

Animal reproduction studies have not been conducted with allergenic extracts. It is also not known whether allergenic extracts can cause fetal harm when administered to a pregnant woman or can affect reproduction capacity.

Controlled studies of hyposensitization with moderate to high doses of allergenic extracts during conception and all trimesters of pregnancy have failed to demonstrate any risk to the fetus or to the mother^4. However, on the basis of histamine’s known ability to contract the uterine muscle, the release of significant amounts of histamine from allergen exposure to skin test overdose should be avoided on theoretical grounds. Therefore, allergenic extracts should be used cautiously in a pregnant woman and only if clearly needed.

Pediatric Use:

Allergenic extracts for diagnostic use have been given safely in infants and young children. Infants have lower skin test reactivity to histamine, as well as common allergens. Skin test reactivity gradually increases to age 6 and plateaus to age 60. Therefore, small skin test reactions should be anticipated in children under age 6.

Geriatric Use:

Skin test reactivity gradually decreases after age 60. Therefore, smaller skin test reactions should be anticipated in adults over age 60.

Nursing Mothers:

It is not known if allergens administered subcutaneously appear in human milk. Because many drugs are excreted in human milk, caution should be exercised when allergenic extracts are administered to a nursing woman.

Carcinogenesis, mutagenesis, impairment of fertility:

Studies in animals have not been performed.

Drug Interactions:

Drugs can interfere with the performance of skin tests^5.

Antihistamines: Response to mediator (histamine) released by allergens is suppressed by antihistamines. The length of suppression varies and is dependent on individual patient, type of antihistamine and length of time the patient has been on antihistamines. The duration of this suppression may be as little as 24 hours (chlorpheniramine) and can be as long as 40 days (astemizole).

Tricyclic Antidepressants: These exert a potent and sustained decrease of skin reactivity to histamine which may last for a few weeks.

Beta2 Agonists: Oral terbutaline and parenteral ephedrine, in general, have been shown to decrease allergen induced wheal.

Dopamine: Intravenous infusion of dopamine may inhibit skin test responses.

Beta Blocking Agents: Propranolol can significantly increase skin test reactivity.

Other Drugs: Short acting steroids, inhaled beta2 agonists, theophylline and cromolyn do not seem to affect skin test response.

ADVERSE REACTIONS

Fatalities from skin testing in the United States have been extensively reviewed by Lockey.^2 Six fatalities were associated with intradermal testing without previous percutaneous testing, and one was associated with a combination of percutaneous (scratch) and intradermal skin testing. With careful attention to dosage and administration, fatal reactions occur infrequently, but it must be remembered that allergenic extracts are highly potent to sensitive individuals and overdosage could result in anaphylactic symptoms. Therefore, it is imperative that physicians administering allergenic extracts for skin testing understand, and be prepared for the treatment of severe reactions.

Local:

Immediate wheal and erythema reactions are to be expected; but if very large, may be the first manifestation of a systemic reaction. In such cases, immediately wipe the test site(s) with sterile gauze or cotton to remove excess allergen.

Systemic Reactions:

Systemic reactions are characterized by one or more of the following symptoms: sneezing, mild to severe generalized urticaria, itching (other than at the skin test site), extensive or generalized edema, wheezing, asthma, dyspnea, cyanosis, hypotension, syncope, and upper airway obstruction. Symptoms may progress to shock and death. Patients should always be observed for at least 20 - 30 minutes after testing.

Volume expanders and vasopressor agents may be required to reverse hypotension. Inhalational bronchodilators and parenteral aminophylline may be required to reverse bronchospasm. Severe airway obstruction unresponsive to bronchodilator may require tracheal intubation and use of oxygen. In the event of a marked systemic reaction, application of a tourniquet above the injection site and the administration of 0.2 mL to 1.0 mL of epinephrine injection (1:1,000) is recommended. Maximum recommended dose for children between 2 and 12 years of age is 0.3 mL. The tourniquet should not be left in place without loosening for 90 seconds every 15 minutes.

Adverse events should be reported via MedWatch (1-800-FDA-1088), Adverse Event Reporting, Food and Drug Administration, 5600 Fishers Lane, Rockville, MD 20852-9787.

OVERDOSAGE

Signs and symptoms of overdose are typically large local and systemic reactions. For management of overdose reactions, refer to the ADVERSE REACTIONS section above.

DOSAGE AND ADMINISTRATION

Parenteral drug products should be inspected visually for particulate matter and discoloration prior to administration, whenever solution and container permit.

Skin test techniques for immediate (Type I) hypersensitivity testing fall into two major categories: percutaneous, and intracutaneous.

Percutaneous techniques:

For percutaneous testing, in general, skin is scratched, punctured or pricked just before the allergen is applied or through a drop of test allergen. There are several devices available for this technique. Refer to the manufacturer or distributor’s circular for specific directions for their use.

In General:

1. It is recommended that the test areas should be placed no closer than 4 - 5 cm apart to avoid interference of reactions when several tests are applied.
2. Skin test areas should be cleansed with alcohol and air dried.
3. Preferably, the allergen should be placed on the volar surface of the forearm, upper arm, or the patient’s back. The patient should be placed in a comfortable position prior to testing.
4. For scratch testing, a sharp, clean, sterile instrument is used to abrade the skin, but not to draw blood. Each scratch should be about 2 - 4 mm in length. A small drop of extract is placed on the surface of the skin.
5. Prick testing: For prick testing, a sharp, sterile instrument is used to puncture the skin slightly, applying it at a 15 - 20° angle to the skin. The instrument is gently raised, “tenting” the skin until it pops out, generally pricking through the drop of allergen. Do not draw blood.
6. For puncture testing, a sharp, clean, sterile instrument must be used. Puncture the skin, through the drop of allergen, perpendicular to the skin. Do not draw blood.

For all of the above techniques, a separate instrument must be used for each patient; if the instrument is to be used to pass through the allergen, to avoid cross-contamination, a separate instrument is to be used for each allergen. The test should be read in 15 minutes, measuring both wheal size and erythema.

Intracutaneous (intradermal) testing:

General: Intradermal testing is more sensitive than percutaneous testing and its specificity is dependent on dose. Intradermal testing is not intended as an initial screen unless used in highly dilute solutions. Intradermal testing is usually reserved for allergens that have demonstrated either negative or equivocal percutaneous skin test response in the face of positive or unclear history.

Intradermal testing of one allergen in several serial dilutions (beginning with the weakest to the more concentrated dilutions) may also be useful in assessing degree of patient sensitivity for the establishment of a safe starting dose for immunotherapy.

Bulk extracts must be diluted for intradermal testing. Use of Sterile Diluent for Allergenic Extracts or Sterile Diluent for Allergenic Extracts Normal Saline with HSA (albumin saline) is recommended. Dilutions should be made with sterile disposable syringes using aseptic technique. Commonly 10 fold dilutions are used to achieve a desired concentration for intradermal testing and continuation of immunotherapy. For example, transferring 0.5 mL of a 10,000 PNU/mL extract into 4.5 mL of diluent will yield 5 mL of extract at 1,000 PNU/mL. For weight volume products, a 1:100 w/v dilution may be prepared from a 1:10 w/v by transferring 0.5 mL of the 1:10 w/v to 4.5 mL of diluent. Prepare as many additional serial dilutions as necessary to reach the appropriate concentration. As a general rule intradermal strength should begin at no higher than 1/100 to 1/1000 of the percutaneous strength that resulted in a negative skin test reaction.

1. It is recommended that the test areas should be spaced no less than 5 cm apart to avoid interference with adjacent allergen or control.
2. Skin should be cleansed with alcohol and air dried.
3. A sterile 1 mL or 1/2 mL syringe with a 26 - 30 gauge needle should be used. A separate sterile syringe should be used for each extract and each patient.
4. Care should be taken to eliminate air bubbles from the syringe prior to injecting the test dose. It is suggested that not more than 6 - 10 allergens of each different type be used at any one time. Very sensitive patients may show rapid response.
5. The skin is held tensely, and the needle is inserted almost parallel to the skin, beveled side up far enough to cover the beveled portion. Slowly inject sufficient extract to make a small bleb of approximately 5 mm in diameter (0.01 - 0.02 mL).
6. Read the test results in 15 minutes.

Selection of the proper strength for intracutaneous testing: A general rule for the prevention of untoward reactions, particularly in extremely sensitive patients, is to screen by percutaneous methods initially, and begin intradermal testing at a strength not more than 1/100 of a negative or equivocal percutaneous reaction.

Controls:

In both percutaneous and intracutaneous tests, a negative control test with diluent alone should be performed because some patients exhibit dermographia, and/or other non-specific irritant responses.

As a positive control in the evaluation of allergenic skin testing, histamine 1 mg/mL (histamine base) should be used for percutaneous testing, and histamine 0.1 mg/mL (histamine base) should be used for intradermal testing.

Interpretation of results:

Patient’s response is graded on the basis of the size of erythema or wheal.^6 General guidelines follow for percutaneous testing, different devices and/or techniques influence the size of the reaction, therefore it is important to refer to the device manufacturer’s or distributor’s instructions when grading reactions.

Percutaneous (prick or scratch) test:

0 No reaction or less than control.

+ Erythema greater than control, smaller than a nickel (21 mm diameter).

++ Erythema greater than a nickel in diameter, no wheal.

+++ Wheal and erythema without pseudopods.

++++ Wheal and erythema with pseudopods.

Intradermal test:

0 No reaction or less than negative control.

+ 3-4 mm wheal with erythema, or erythema alone larger than a nickel (21 mm diameter).

++ 4-8 mm wheal and erythema, without pseudopods.

+++ Over 8 mm wheal and erythema without pseudopods.

++++ Wheal and erythema with pseudopods.

HOW SUPPLIED

For scratch and prick testing: 5 mL dropper applicator vials in 50% v/v glycerin or 10mL stoppered vial in 50% v/v glycerin. Available individually and in a complete set of the most common allergens. Available in either Protein Nitrogen Units (PNU/mL) or weight to volume (w/v).

For intracutaneous testing: 5 mL sterile vials, aqueous based, individually and in a complete set of the most common allergens. Available in either Protein Nitrogen Units (PNU/mL) or weight to volume (w/v).

Histatrol® Positive skin test control - histamine. 1 mg/mL and 0.1 mg/mL histamine base.

See Product Catalog for specific diagnostic concentrations available.

STORAGE

To maintain stability of allergenic extracts, proper storage conditions are essential. Bulk concentrates and diluted extracts are to be stored at 2º to 8ºC even during use. Bulk or diluted extracts are not to be frozen. Do not use after the expiration date shown on the vial label.

REFERENCES

1. Holgate, S.T., Robinson, C. and Church, M.K. Mediators of immediate hypersensitivity. In Middleton et al: Allergy Principles and Practice, St. Louis, 1988, C.V. Mosby, p 135.
2. Lockey, R.F., et al. Fatalities from immunotherapy (IT) and skin testing (ST). J. Allergy Clin. Immunol. 1987: 79: 660.
3. Reid, M.J. et al. Survey of fatalities from skin testing and immunotherapy. 1985-1989. J. Allergy Clin Immunol. 1993; 92:6.
4. DeBuske L. M. et al. Special problems regarding Allergen Immunotherapy in Immunology and Allergy Clinics of North America, Greenburger, P.A. Ed. February 1992; 145-149.
5. Bousquet, J. In vivo methods for the study of allergy: skin test, techniques and interpretation. In: Middleton et al.: Allergy Principles and Practice 3rd Ed. St. Louis: CV Mosby, 1988:167.
6. Freedman, S.O. Asthma and Allergic Rhinitis II. Clinical Aspects, in Freedman and Gold Clinical Immunology 2nd Ed. New York: Harper & Row, 1976: 131.

Revised February 2023 No. 112S

© ALK-Abelló, Inc.

Distributed in Canada by:
ALK-Abelló Pharmaceuticals, Inc.
#35-151 Brunel Road
Mississauga, Ontario
Canada L4Z 2H6

PRINCIPAL DISPLAY PANEL

ALLERGENIC EXTRACT
DIN 00299987
5mL sterile multiple dose vial
FOR PERCUTANEOUS TESTING ONLY